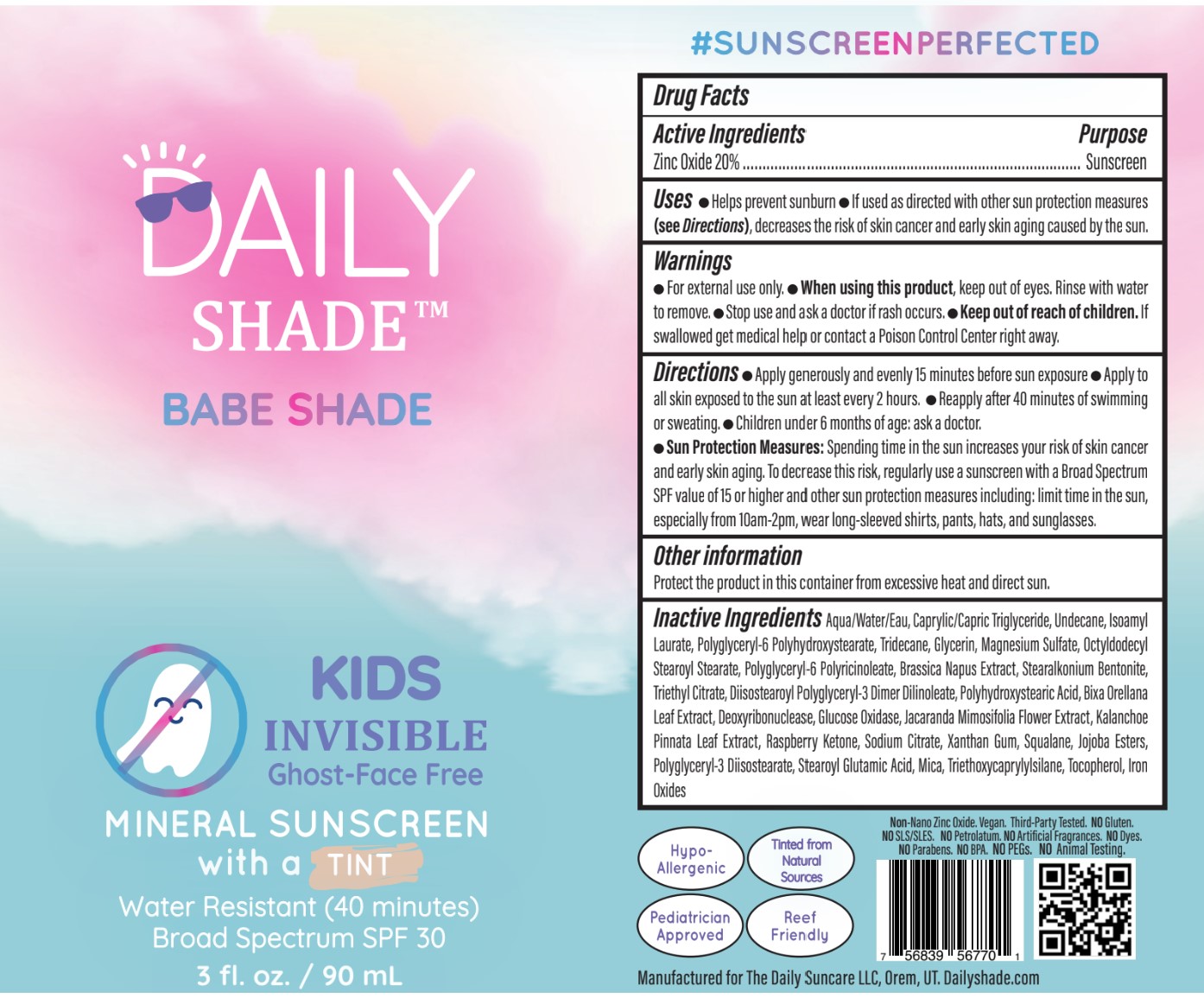 DRUG LABEL: Mineral Sunscreen
NDC: 84380-001 | Form: LOTION
Manufacturer: The Daily Suncare LLC, DBA Daily Shade
Category: otc | Type: HUMAN OTC DRUG LABEL
Date: 20260128

ACTIVE INGREDIENTS: ZINC OXIDE 20 g/100 g
INACTIVE INGREDIENTS: UNDECANE; DIISOSTEAROYL POLYGLYCERYL-3 DIMER DILINOLEATE; 4-(P-HYDROXYPHENYL)-2-BUTANONE; SODIUM CITRATE; TOCOPHEROL; FERRIC OXIDE YELLOW; POLYGLYCERYL-6 STEARATE; JACARANDA MIMOSIFOLIA WHOLE; MICA; TRIETHOXYCAPRYLYLSILANE; GLYCERIN; FERRIC OXIDE RED; TRIETHYL CITRATE; TRIDECANE; KALANCHOE PINNATA WHOLE; MEDIUM-CHAIN TRIGLYCERIDES; XANTHAN GUM; POLYGLYCERYL-3 DIISOSTEARATE; BRASSICA NAPUS WHOLE; JOJOBA OIL, RANDOMIZED; WATER; GLUCOSE OXIDASE; SQUALANE; MAGNESIUM SULFATE, UNSPECIFIED FORM; BIXA ORELLANA LEAF; POLYHYDROXYSTEARIC ACID (2300 MW); STEAROYL GLUTAMIC ACID; FERROSOFERRIC OXIDE; OCTYLDODECYL STEAROYL STEARATE; POLYGLYCERYL-6 POLYRICINOLEATE; ISOAMYL LAURATE; STEARALKONIUM BENTONITE

ACTIVE INGREDIENT

Zinc Oxide 20%

DOSAGE AND ADMINISTRATION

Topical Lotion

PURPOSE

Sunscreen

INDICATIONS AND USAGE

Helps prevent sunburn. If used as directed with other sun protection measures (see Directions), decreases the risk of skin cancer and early skin aging caused by the sun.

INSTRUCTIONS FOR USE

Apply generously and evenly 15 minutes before sun exposure. Apply to all skin exposed to the sun at least every 2 hours. Reapply after 40 minutes of swimming or sweating. Children under 6 months of age: ask a doctor.

Sun Protection Measures: Spending time in the sun increases risk of skin cancer and early skin aging. To decrease this risk, regularly use a sunscreen with a Broad Spectrum SPF value of 15 or highre and other sun protection measures including: limit time in the sun, especially from 10am-2pm, wear long-sleeved shirts, pants, hats, and sunglasses.

WARNINGS

For external use only. When using this product, keep out of eyes. Rinse with water to remove. Stop use and ask a doctor if rash occurs. Keep out of reach of children. If swallowed get medical help or contact a Poison Control Center right away.

Keep out of reach of children. If swallowed, get medical help or contact a Poison Control Center right away.

Stop use and ask a doctor if rash occurs.

OTHER SAFETY INFORMATION

Protect the product in this container from excessive heat and direct sun.

Stop use and ask a doctor if rash occurs. Children under 6 months of age: ask a doctor

INACTIVE INGREDIENT

Aqua/Water/Eau, Caprylic/Capric Triglyceride, Undecane, Isoamyl Laurate, Polyglyceryl-6 Polyhydroxystearate, Tridecane, Glycerin, Magnesium Sulfate, Octyldodecyl Stearoyl Stearate, Polyglyceryl-6 Polyricinoleate,Brassica Napus Extract, Stearalkonium Bentonite, Triethyl Citrate, Diisostearoyl Polyglyceryl-3 Dimer Dilinoleate, Polyhydroxystearic Acid, Bixa Orellana Leaf Extract, Deoxyribonuclease, Glucose Oxidase, Jacaranda Mimosifolia Flower Extract, Kalanchoe Pinnata Leaf Extract, Raspberry Ketone, Sodium Citrate, Xanthan Gum, Squalane, Jojoba Esters, Polyglyceryl-3 Diisostearate, Stearoyl Glutamic Acid, Mica, Triethoxycaprylylsilane, Tocopherol, Iron Oxides